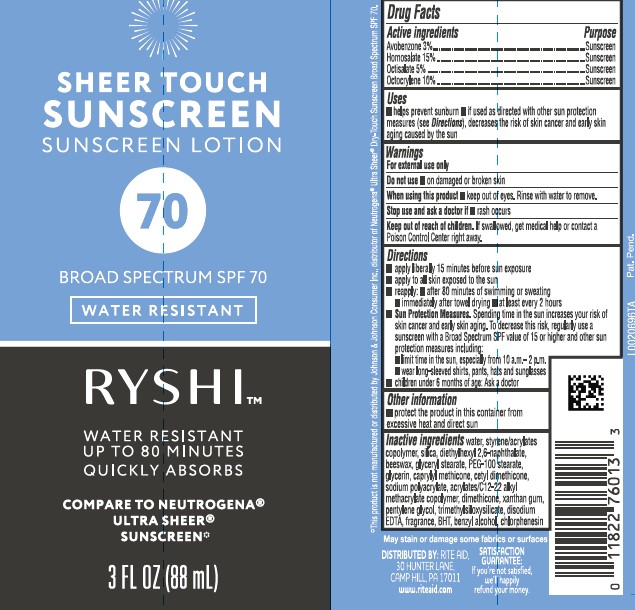 DRUG LABEL: sheer
NDC: 11822-1978 | Form: LOTION
Manufacturer: Rite Aid Corporation
Category: otc | Type: HUMAN OTC DRUG LABEL
Date: 20260202

ACTIVE INGREDIENTS: AVOBENZONE 30 mg/1 mL; HOMOSALATE 150 mg/1 mL; OCTISALATE 50 mg/1 mL; OCTOCRYLENE 100 mg/1 mL
INACTIVE INGREDIENTS: WATER; STYRENE/ACRYLAMIDE COPOLYMER (500000 MW); SILICON DIOXIDE; DIETHYLHEXYL 2,6-NAPHTHALATE; YELLOW WAX; GLYCERYL STEARATE SE; PEG-100 STEARATE; GLYCERIN; CAPRYLYL TRISILOXANE; CETYL DIMETHICONE 150; SODIUM POLYACRYLATE (2500000 MW); BUTYL ACRYLATE/METHYL METHACRYLATE/METHACRYLIC ACID COPOLYMER (18000 MW); DIMETHICONE; XANTHAN GUM; PENTYLENE GLYCOL; TRIMETHYLSILOXYSILICATE (M/Q 0.6-0.8); EDETATE DISODIUM ANHYDROUS; BUTYLATED HYDROXYTOLUENE; BENZYL ALCOHOL; CHLORPHENESIN

RYSHI 978.000/978AA
Sheer Touch Sunscreen SPF 70

active ingredients

Avobenzone 3%

Homosalate 15%

Octisalate 5%

Octocrylene 10%

Purpose

Sunscreen

Uses

- helps prevent sunburn
- if used as directed with other sun protection measures (See Directions), decreases the risk of skin cancer and early skin aging caused by the sun

Warnings

For external use only

Do not use

- on damaged or broken skin

When using this product

- keep out of eyes. Rinse with water to remove.

Stop use and ask a doctor if

- rash occurs

Keep out of reach of children.

If swallowed, get medical help or contact a Poison Control right away.

Directions

- apply liberaly 15 minutes before sun exposure
- apply to all skin exposed to the sun
- reapply:
- after 80 minutes of swimming or sweating
- immediately after towel drying
- at least every 2 hours
- Sun Protection Measures. Spending time in the sun increases your risk of skin cancer and early skin aging. To decrease this risk, regularly use a sunscreen with Broad Spectrum SPF value of 15 or higher and other sun protection measures including:
- limit time in the sun, especialy from 10 a.m. -2 p.m.
- wear long-sleeved shirts, pants, hats and sunglasses
- children under 6 months of age: Ask a doctor

Other information

- protect the product in this container from excessive heat and direct sun

inactive ingredients

water, styrene/acrylates copolymer, silica, diethylhexyl 2,6-naphthalate, beeswax, glyceryl stearate, PEG-100 stearate, glycerin, caprylyl methicone, cetyl dimethicone, sodium polyacrylate, acrylates/C12-22 alkyl methacrylate copolymer, dimethicone, xanthan gum, pentylene glycol, trimethylsiloxysilicate, disodium EDTA, fragrance, BHT, benzyl alcohol, chlorphenesin

Disclaimers

May stain or damage some fabrics or surfaces

*This product is not manufactured or distributed by Johnson & Johnson Consumer Inc., distributor of NeutrogenaUltra Sheer Dry-Touch Sunscreen Broad Spectrum SPF 70.

ADVERSE REACTION

DISTRIBUTED BY: RITE AID

30 HUNTER LANE

CAMP HILL, PA 17011

www.riteaid.com

SATISFACTION GUARANTEE:

If you're not satisfied, we'll happily refund your money.

principal display panel

SHEER TOUCH SUNSCREEN

SUNSCREEN LOTION

70

BROAD SPECTRUM SPF 70

WATER RESISTANT

RYSHITM

WATER RESISTANT

UP TO 80 MINUTES

QUICKLY ABSORBS

COMPARE TO NEUTROGENA®ULTRA SHEER SUNSCREEN*

3 FL OZ (88 mL)